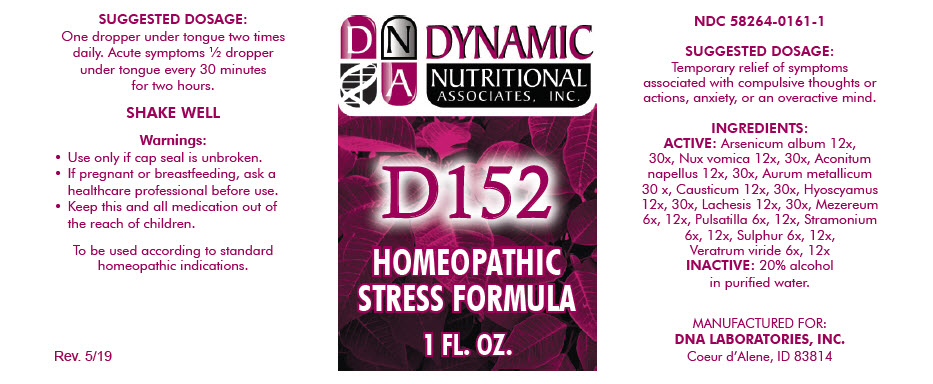 DRUG LABEL: D-152
NDC: 58264-0161 | Form: SOLUTION
Manufacturer: DNA Labs, Inc.
Category: homeopathic | Type: HUMAN OTC DRUG LABEL
Date: 20250113

ACTIVE INGREDIENTS: CAUSTICUM 12 [hp_X]/1 mL; HYOSCYAMUS NIGER LEAF 12 [hp_X]/1 mL; LACHESIS MUTA WHOLE 12 [hp_X]/1 mL; DAPHNE MEZEREUM WHOLE 6 [hp_X]/1 mL; ANEMONE PULSATILLA 6 [hp_X]/1 mL; SULFUR 6 [hp_X]/1 mL; VERATRUM VIRIDE WHOLE 6 [hp_X]/1 mL; ARSENIC TRIOXIDE 12 [hp_X]/1 mL; STRYCHNOS NUX-VOMICA SEED 12 [hp_X]/1 mL; ACONITUM NAPELLUS 12 [hp_X]/1 mL; GOLD 30 [hp_X]/1 mL
INACTIVE INGREDIENTS: ALCOHOL; WATER

D-152

NDC 58264-0161-1

INDICATIONS AND USAGE

SUGGESTED DOSAGE

Temporary relief of symptoms associated with compulsive thoughts or actions, anxiety, or an overactive mind.

INGREDIENTS

ACTIVE

Arsenicum album 12x, 30x, Nux vomica 12x, 30x, Aconitum napellus 12x, 30x, Aurum metallicum 30 x, Causticum 12x, 30x, Hyoscyamus 12x, 30x, Lachesis 12x, 30x, Mezereum 6x, 12x, Pulsatilla 6x, 12x, Stramonium 6x, 12x, Sulphur 6x, 12x, Veratrum viride 6x, 12x

INACTIVE

20% alcohol in purified water.

SUGGESTED DOSAGE

One dropper under tongue two times daily. Acute symptoms ½ dropper under tongue every 30 minutes for two hours.

STORAGE AND HANDLING

SHAKE WELL

Warnings

- Use only if cap seal is unbroken.

PREGNANCY OR BREAST FEEDING

- If pregnant or breastfeeding, ask a healthcare professional before use.

KEEP OUT OF REACH OF CHILDREN

- Keep this and all medication out of the reach of children.

To be used according to standard homeopathic indications.

PRINCIPAL DISPLAY PANEL - 1 FL. OZ. Bottle Label

DYNAMIC
NUTRITIONAL
ASSOCIATES, INC.

D 152

HOMEOPATHIC
STRESS FORMULA

1 FL. OZ.